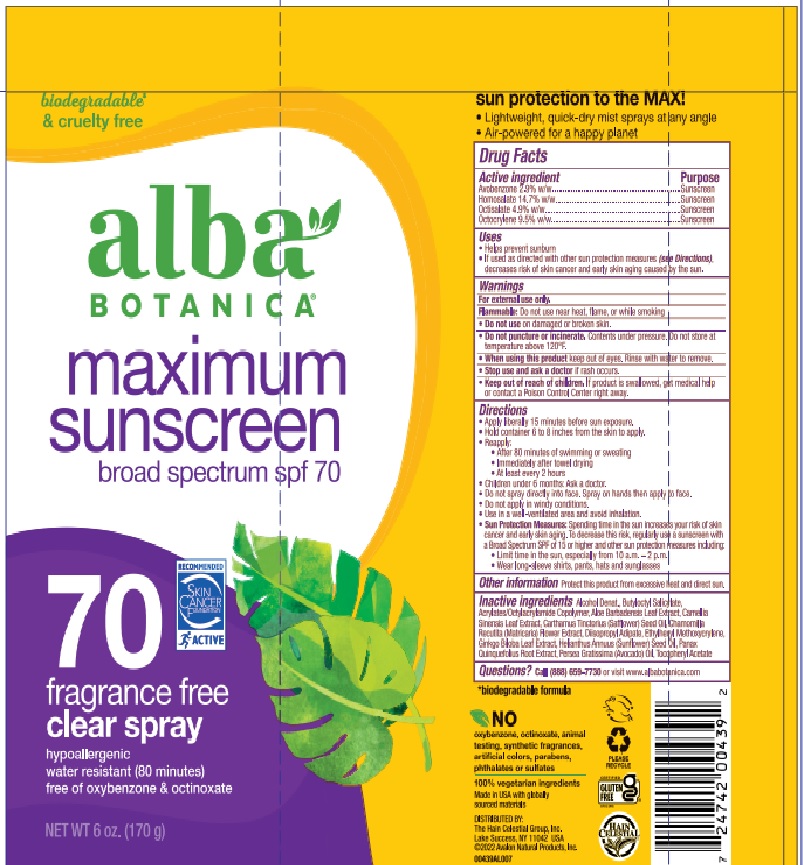 DRUG LABEL: Alba Botanica Maximum Sunscreen SPF 70
NDC: 61995-3035 | Form: SPRAY
Manufacturer: Hain Celestial Group, Inc
Category: otc | Type: HUMAN OTC DRUG LABEL
Date: 20231116

ACTIVE INGREDIENTS: OCTOCRYLENE 9.5 g/100 mL; OCTISALATE 4.9 g/100 mL; AVOBENZONE 2.9 g/100 mL; HOMOSALATE 14.7 g/100 mL
INACTIVE INGREDIENTS: PANAX GINSENG ROOT OIL; ALCOHOL; BUTYLOCTYL SALICYLATE; AVOCADO OIL; SUNFLOWER OIL; ACRYLATE/ISOBUTYL METHACRYLATE/N-TERT-OCTYLACRYLAMIDE COPOLYMER (75000 MW); ALOE VERA LEAF; MATRICARIA RECUTITA; SAFFLOWER OIL; CAMELLIA OIL; DIISOPROPYL ADIPATE; GINKGO; .ALPHA.-TOCOPHEROL ACETATE; ETHYLHEXYL METHOXYCRYLENE

Alba Botanica Maximum Sunscreen SPF 70 Spray

ACTIVE INGREDIENT

AVOBENZONE 2.9%

HOMOSALATE 14.7%

OCTISALATE 4.9%

OCTOCRYLENE 9.5%

INACTIVE INGREDIENT

Alcohol Denat., Butyloctyl Salicylate, Acrylates/Octylacrylamide Copolymer, Aloe Barbadensis Leaf Extract, Camellia Sinensis Leaf Extract, Carthamus Tinctorius (Safflower) Seed Oil, Chamomilla Recutita (Matricaria) Flower Extract, Diisopropyl Adipate, Ethylhexyl Methoxycrylene, Ginkgo Biloba Leaf Extract, Helianthus Annuus (Sunflower) Seed Oil, Panax Quinquefolius Root Extract, Persea Gratissima (Avocado) Oil, Tocopheryl Acetate

PURPOSE

Sunscreen. Helps prevent sunburn

INDICATIONS AND USAGE

● Hold container 4 to 6 inches/ from skin to apply ● Spray liberally/generously and spread evenly by hand 15 minutes before sun exposure. Do not spray directly onto face; spray on hands, then apply to face. Do not apply in windy conditions. Use in a well-ventilated area and avoid inhaling or exposing others to spray. ● reapply: ● at least every 2 hours ● after 40 minutes of swimming or sweating
● immediately after towel drying. Sun Protection Measures: Spending time in the sun increases your risk of skin cancer and early skin aging. To decrease this risk, regularly use sunscreen with a Broad Spectrum SPF value of 15 or higher and other sun protection measures including: ■ limit time in the sun, especially from 10 am - 2 pm/ 11 a.m. – 3 p.m ■ wear long-sleeved shirts, pants, hats, and sunglasses. ● For use on children under 6 months of age, ask a doctor.

WARNINGS

For external use only.

Do not use on damaged or broken skin.

When using this product avoid contact with eyes.If contact occurs, rinse thoroughly with water.

Stop use and ask a doctor if rash occurs.

Keep out of reach of children. If swallowed, get medical help or contact a Poison Control Center right away